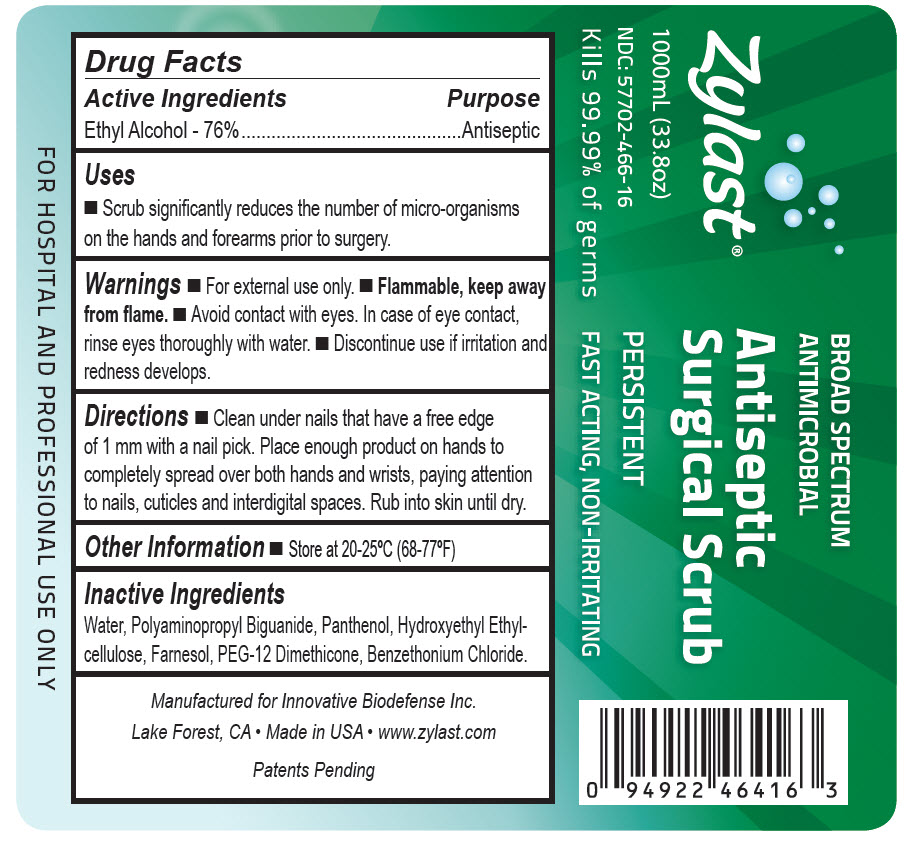 DRUG LABEL: Zylast Antiseptic Surgical Scrub
NDC: 57702-466 | Form: LIQUID
Manufacturer: Bocchi Laboratories Inc.
Category: otc | Type: HUMAN OTC DRUG LABEL
Date: 20140224

ACTIVE INGREDIENTS: ALCOHOL 0.76 mL/1 mL
INACTIVE INGREDIENTS: FARNESOL; WATER; POLIHEXANIDE; PANTHENOL; BENZETHONIUM CHLORIDE

Zylast Antiseptic Surgical Scrub
Drug Facts

Active Ingredients

Ethyl alcohol 76%

Purpose

Antiseptic

Uses

- Scrub significantly reduces the number of micro-organisms on the hands and forearms prior to surgery.

Warnings

- For external use only.
- Flammable. Keep away from flame.
- Avoid contact with eyes. In case of eye contact, rinse eyes thoroughly with water.
- Discontinue use if irritation and redness develops.

Directions

- Clean under nails that have a free edge of 1 mm with a nail pick. Place enough product on hands to completely spread over both hands and wrists, paying attention to nails, cuticles and interdigital spaces. Rub into skin until dry.

Other Information

- Store at 20-25°C (68-77°F)

Inactive ingredients

Water, Polyaminopropyl Biguanide, Panthenol, Hydroxyethyl Ethylcellulose, Farnesol, PEG- 12 Dimethicone, Benzethonium Chloride.

Package/Label Principal Display Panel

NDC 57702-466-16
Zylast
Antiseptic
Surgical Scrub
1000mL (33.8oz)